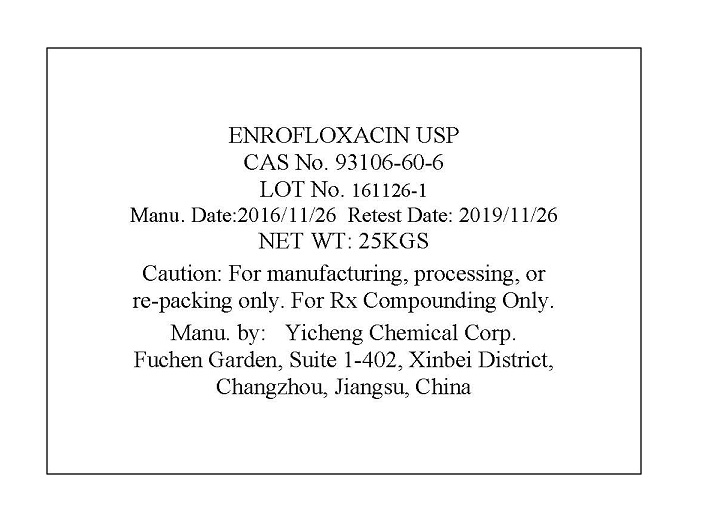 DRUG LABEL: ENROFLOXACIN
NDC: 67995-0154 | Form: POWDER
Manufacturer: Yicheng Chemical Corp.
Category: other | Type: BULK INGREDIENT
Date: 20170711

ACTIVE INGREDIENTS: ENROFLOXACIN 1 kg/1 kg

ENROFLOXACIN USP-Label